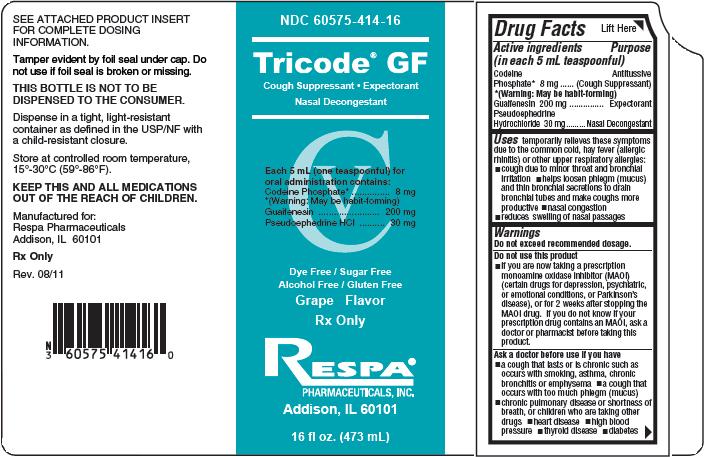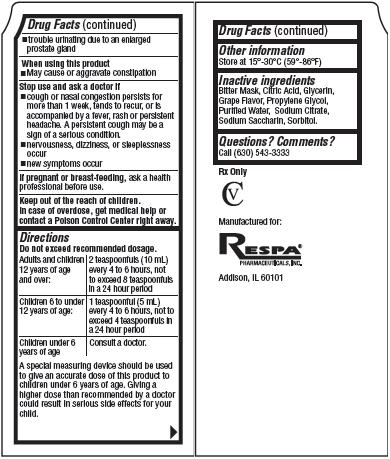 DRUG LABEL: Tricode
NDC: 60575-414 | Form: LIQUID
Manufacturer: Respa Pharmaceuticals, Inc.
Category: otc | Type: HUMAN OTC DRUG LABEL
Date: 20110909
DEA Schedule: CV

ACTIVE INGREDIENTS: Codeine Phosphate 8 mg/5 mL; Guaifenesin 200 mg/5 mL; Pseudoephedrine Hydrochloride 30 mg/5 mL
INACTIVE INGREDIENTS: Citric Acid; Glycerin; Propylene Glycol; Water; Sodium Citrate; Saccharin Sodium; Sorbitol

Tricode GF

Drug Facts

Active ingredients
(in each 5 mL teaspoonful)
Codeine Phosphate* 8 mg
*(Warning: May be habit-forming)
Guaifenesin 200 mg
Pseudoephedrine Hydrochloride 30 mg

Purpose

Antitussive (Cough Suppressant)
Expectorant
Nasal Decongestant

Uses

temporarily relieves these symptoms due to the common cold, hay fever (allergic rhinitis) or other upper respiratory allergies:

- cough due to minor throat and bronchial irritation
- helps loosen phlegm (mucus) and thin bronchial secretions to drain bronchial tubes and make coughs more productive
- nasal congestion
- reduces swelling of nasal passages

Warnings

Do not exceed recommended dosage.

Do not use this product

- if you are now taking a prescription monoamine oxidase inhibitor (MAOI) (certain drugs for depression, psychiatric, or emotional conditions, or Parkinson's disease), or for 2 weeks after stopping the MAOI drug. If you do not know if your prescription drug contains an MAOI, ask a doctor or pharmacist before taking this product.

Ask a doctor before use if you have

- a cough that lasts or is chronic such as occurs with smoking, asthma, chronic bronchitis or emphysema
- a cough that occurs with too much phlegm (mucus)
- chronic pulmonary disease or shortness of breath, or children who are taking other drugs
- heart disease
- high blood pressure
- thyroid disease
- diabetes
- trouble urinating due to an enlarged prostate gland

When using this product

- May cause or aggravate constipation

Stop use and ask a doctor if

- cough or nasal congestion persists for more than 1 week, tends to recur, or is accompanied by a fever, rash or persistent headache. A persistent cough may be a sign of a serious condition.
- nervousness, dizziness, or sleeplessness occur
- new symptoms occur

If pregnant or breast-feeding,

ask a health professional before use.

Keep out of the reach of children.

In case of accidental overdose, get medical help or contact a Poison Control Center right away.

Directions

Do not exceed recommended dosage.

Adults and children 12 years of age and over: | 2 teaspoonfuls (10 mL) every 4 to 6 hours, not to exceed 8 teaspoonfuls in a 24 hour period
Children 6 to under 12 years of age: | 1 teaspoonful (5 mL) every 4 to 6 hours, not to exceed 4 teaspoonfuls in a 24 hour period
Children under 6 years of age | Consult a doctor.

A special measuring device should be used to give an accurate dose of this product to children under 6 years of age. Giving a higher dose than recommended by a doctor could result in serious side effects for your child.

Other information

Store at 15°- 30°C (59°- 86°F)

Inactive ingredients

Bitter Mask, Citric Acid, Glycerin, Grape Flavor, Propylene Glycol, Purified Water, Sodium Citrate, Sodium Saccharin, Sorbitol.

Questions? Comments?

Call (630) 543-3333
Rx Only
CV
Manufactured for:
RESPA®
PHARMACEUTICALS, INC.
Addison, IL 60101

Product Packaging

The packaging below represents the labeling currently used:
Principal display panel and side panel for 473 mL label:
NDC 60575-414-16
__________________________________________
Tricode® GF
Cough Suppressant·Expectorant
Nasal Decongestant
__________________________________________
CV
Each 5 mL (one teaspoonful) for oral administration
contains:
Codeine Phosphate*.......................................8 mg
*(Warning: May be habit-forming)
Guaifenesin................................................200 mg
Pseudoephedrine HCl....................................30 mg
Dye Free / Sugar Free
Alcohol Free / Gluten Free
Grape Flavor
Rx Only
RESPA®
PHARMACEUTICALS, INC.
Addison, IL 60101
16 fl oz. (473 mL)
SEE ATTACHED PRODUCT INSERT FOR COMPLETE
DOSING INFORMATION.
Tamper evident by foil seal under cap. Do not use if
foil seal is broken or missing.
THIS BOTTLE IS NOT TO BE DISPENSED TO
THE CONSUMER.
Dispense in a tight, light-resistant container as defined
in the USP/NF with a child-resistant closure.
Store at controlled room temperature, 15°- 30°C (59°- 86°F).
KEEP THIS AND ALL MEDICATIONS OUT OF THE
REACH OF CHILDREN.
Manufactured for:
Respa Pharmaceuticals
Addison, IL 60101
Rx Only
Rev. 08/11